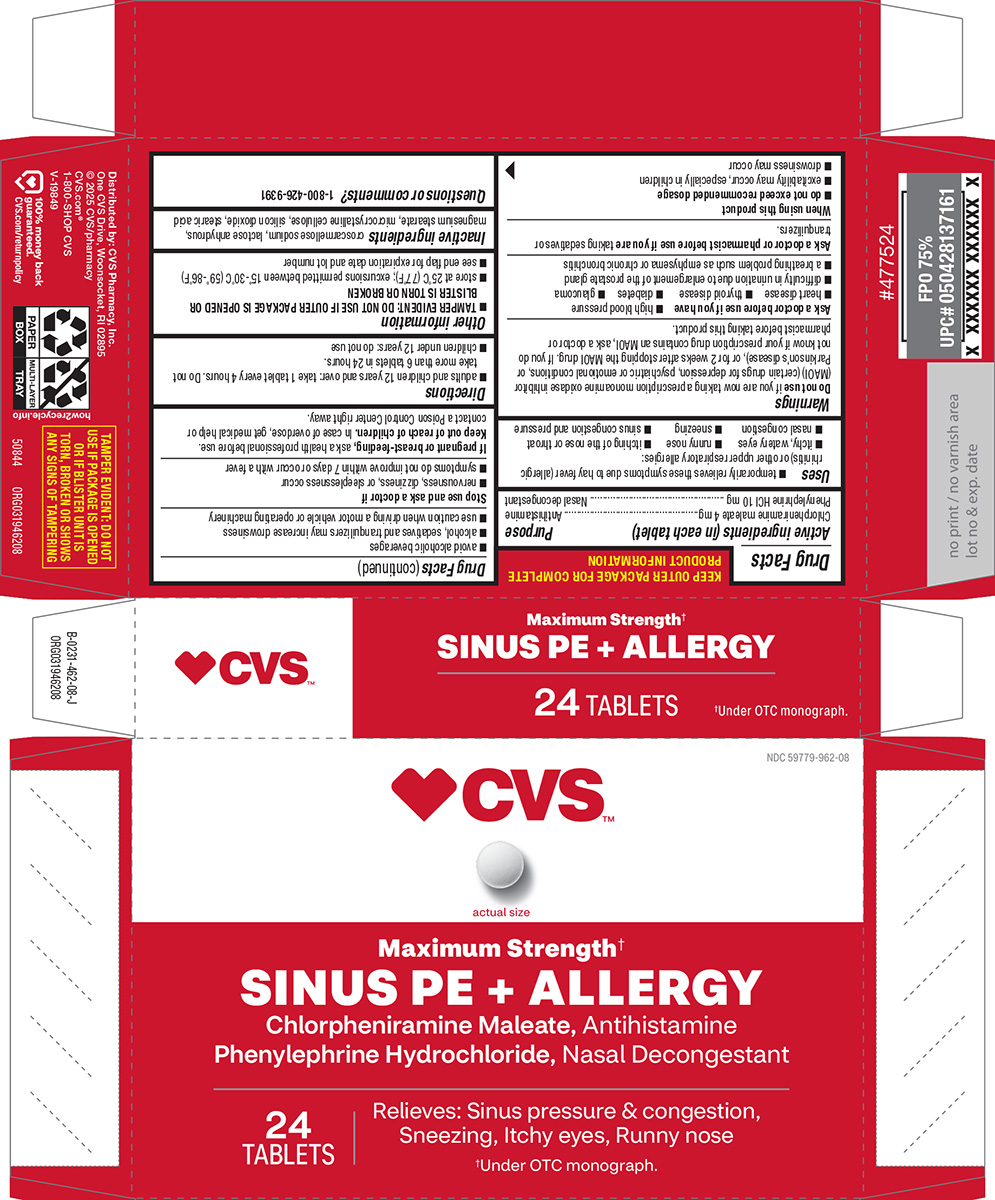 DRUG LABEL: Sinus PE plus Allergy
NDC: 59779-962 | Form: TABLET
Manufacturer: CVS Pharmacy
Category: otc | Type: HUMAN OTC DRUG LABEL
Date: 20251029

ACTIVE INGREDIENTS: CHLORPHENIRAMINE MALEATE 4 mg/1 1; PHENYLEPHRINE HYDROCHLORIDE 10 mg/1 1
INACTIVE INGREDIENTS: CROSCARMELLOSE SODIUM; ANHYDROUS LACTOSE; MAGNESIUM STEARATE; MICROCRYSTALLINE CELLULOSE; SILICON DIOXIDE; STEARIC ACID

CVS 44-462

Active ingredients (in each tablet)

Chlorpheniramine maleate 4 mg
Phenylephrine HCl 10 mg

Purpose

Antihistamine
Nasal decongestant

Uses

- temporarily relieves these symptoms due to hay fever (allergic rhinitis) or other upper respiratory allergies:
  - itchy, watery eyes
  - runny nose
  - itching of the nose or throat
  - nasal congestion
  - sneezing
  - sinus congestion and pressure

Warnings

Do not use

if you are now taking a prescription monoamine oxidase inhibitor (MAOI) (certain drugs for depression, psychiatric or emotional conditions, or Parkinson’s disease), or for 2 weeks after stopping the MAOI drug. If you do not know if your prescription drug contains an MAOI, ask a doctor or pharmacist before taking this product.

Ask a doctor before use if you have

- high blood pressure
- heart disease
- thyroid disease
- diabetes
- glaucoma
- difficulty in urination due to enlargement of the prostate gland
- a breathing problem such as emphysema or chronic bronchitis

Ask a doctor or pharmacist before use if you are

taking sedatives or tranquilizers.

When using this product

- do not exceed recommended dosage
- excitability may occur, especially in children
- drowsiness may occur
- avoid alcoholic beverages
- alcohol, sedatives and tranquilizers may increase drowsiness
- use caution when driving a motor vehicle or operating machinery

Stop use and ask a doctor if

- nervousness, dizziness, or sleeplessness occur
- symptoms do not improve within 7 days or occur with a fever

If pregnant or breast-feeding,

ask a health professional before use.

Keep out of reach of children.

In case of overdose, get medical help or contact a Poison Control Center right away.

Directions

- adults and children 12 years and over: take 1 tablet every 4 hours. Do not take more than 6 tablets in 24 hours.
- children under 12 years: do not use

Other information

- TAMPER EVIDENT: DO NOT USE IF OUTER PACKAGE IS OPENED OR BLISTER IS TORN OR BROKEN
- store at 25°C (77°F); excursions permitted between 15°-30°C (59°-86°F)
- see end flap for expiration date and lot number

Inactive ingredients

croscarmellose sodium, lactose anhydrous, magnesium stearate, microcrystalline cellulose, silicon dioxide, stearic acid

Questions or comments?

1-800-426-9391

Principal display panel

♥︎CVS™

NDC 59779-962-08

actual size

Maximum Strength†
SINUS PE + ALLERGY
Chlorpheniramine Maleate, Antihistamine
Phenylephrine Hydrochloride, Nasal Decongestant

Relieves: Sinus pressure & congestion,
Sneezing, Itchy eyes, Runny nose

†Under OTC monograph.

24
TABLETS

TAMPER EVIDENT: DO NOT
USE IF PACKAGE IS OPENED
OR IF BLISTER UNIT IS
TORN, BROKEN OR SHOWS
ANY SIGNS OF TAMPERING

50844 ORG031946208

Distributed by: CVS Pharmacy, Inc.
One CVS Drive, Woonsocket, RI 02895
© 2025 CVS/pharmacy
CVS.com®
1-800-SHOP CVS
V-19849

♥︎100% money back
guaranteed.
CVS.com/returnpolicy

CVS 44-462